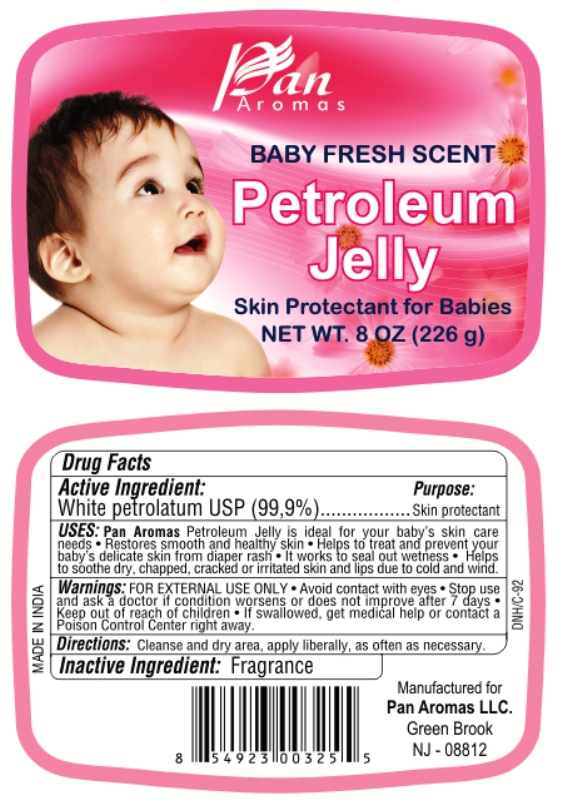 DRUG LABEL: Baby Fresh Scent Petroleum
NDC: 50346-002 | Form: JELLY
Manufacturer: Pan Aromas LLC
Category: otc | Type: HUMAN OTC DRUG LABEL
Date: 20120526

ACTIVE INGREDIENTS: PETROLATUM 0.99 g/1 g

BABY FRESH SCENT PETROLEUM JELLY

Active ingredient

White petrolatum USP (99.9 %)

Purpose

Skin protectant

Uses

- Ideal for your baby’s skin care needs
- Restores smooth and healthy skin
- Helps to treat and prevent your baby’s delicate skin from diaper rash
- It works to seal out wetness
- Helps to soothe dry, chapped, cracked or irritated skin and lips due to cold and wind

Warnings

For external use only.

Do not use

over deep or puncture wounds, infections or lacerations. Ask a doctor.

When using this product

avoid contact with eyes.

Stop use and ask a doctor

if condition worsens or does not improve after 7 days.

Keep out of reach of children

If swallowed get medical help or contact a Poison Control Center right away.

Directions

Cleanse and dry area, apply liberally, as often as necessary.

Inactive ingredients

Fragrance

PRINCIPAL DISPLAY PANEL

BABY FRESH SCENT

PETROLEUM JELLY

SKIN PROTECTANT FOR BABIES

NET WT. 8 OZ (226 g)